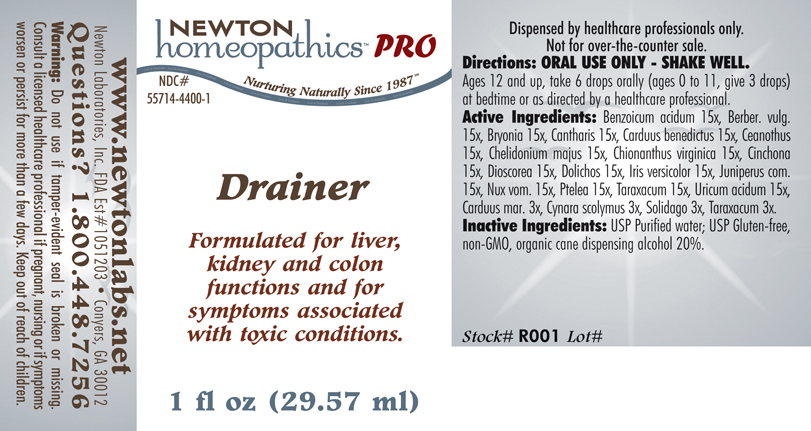 DRUG LABEL: Drainer 
NDC: 55714-4400 | Form: LIQUID
Manufacturer: Newton Laboratories, Inc.
Category: homeopathic | Type: HUMAN PRESCRIPTION DRUG LABEL
Date: 20110601

ACTIVE INGREDIENTS: Benzoic Acid 15 [hp_X]/1 mL; Berberis Vulgaris Root Bark 15 [hp_X]/1 mL; Bryonia Alba Root 15 [hp_X]/1 mL; Lytta Vesicatoria 15 [hp_X]/1 mL; Cnicus Benedictus 15 [hp_X]/1 mL; Ceanothus Americanus Leaf 15 [hp_X]/1 mL; Chelidonium Majus 15 [hp_X]/1 mL; Chionanthus Virginicus Bark 15 [hp_X]/1 mL; Cinchona Officinalis Bark 15 [hp_X]/1 mL; Dioscorea Villosa Tuber 15 [hp_X]/1 mL; Mucuna Pruriens Fruit Trichome 15 [hp_X]/1 mL; Iris Versicolor Root 15 [hp_X]/1 mL; Juniper 15 [hp_X]/1 mL; Strychnos Nux-vomica Seed 15 [hp_X]/1 mL; Ptelea Trifoliata Bark 15 [hp_X]/1 mL; Taraxacum Officinale 15 [hp_X]/1 mL; Uric Acid 15 [hp_X]/1 mL; Silybum Marianum Seed 3 [hp_X]/1 mL; Cynara Scolymus Leaf 3 [hp_X]/1 mL; Solidago Virgaurea Flowering Top 3 [hp_X]/1 mL; Taraxacum Officinale 3 [hp_X]/1 mL

Drainer

PRODUCT NAME & INDICATIONS SECTION

Drainer Formulated for liver, kidney and colon functions and for symptoms associated with toxic conditions.

DIRECTION SECTION

Directions: ORAL USE ONLY - SHAKE WELL. Ages 12 and up, take 6 drops orally (ages 0 to 11, give 3 drops) at bedtime or as directed by a healthcare professional.

ACTIVE INGREDIENT SECTION

Benzoicum acidum 15x, Berber. vulg. 15x, Bryonia 15x, Cantharis 15x, Carduus benedictus 15x, Ceanothus 15x, Chelidonium majus 15x, Chionanthus virginica 15x, Cinchona 15x, Dioscorea 15x, Dolichos 15x, Iris versicolor 15x, Juniperus com.15x, Nux vom. 15x, Ptelea 15x, Taraxacum 15x, Uricum acidum 15x,Carduus mar. 3x, Cynara scolymus 3x, Solidago 3x, Taraxacum 3x.

INACTIVE INGREDIENT SECTION

Inactive Ingredients: USP Purified Water; USP Gluten-free, non-GMO, organic cane dispensing alcohol 20%.

QUESTIONS? SECTION

www.newtonlabs.net Newton Laboratories, Inc. FDA Est # 1051203 -Conyers, GA 30012
Questions? 1.800.448.7256

WARNINGS SECTION

Warning: Do not use if tamper - evident seal is broken or missing. Consult a licensed healthcare professional if pregnant, nursing or if symptoms worsen or persist for more than a few days. Keep out of reach of children.

OTC - PREGNANCY OR BREAST FEEDING SECTION

Consult a licensed healthcare professional if pregnant or nursing or if symptoms worsen or persist for more than a few days.

OTC - KEEP OUT OF REACH OF CHILDREN SECTION

Keep out of reach of children.